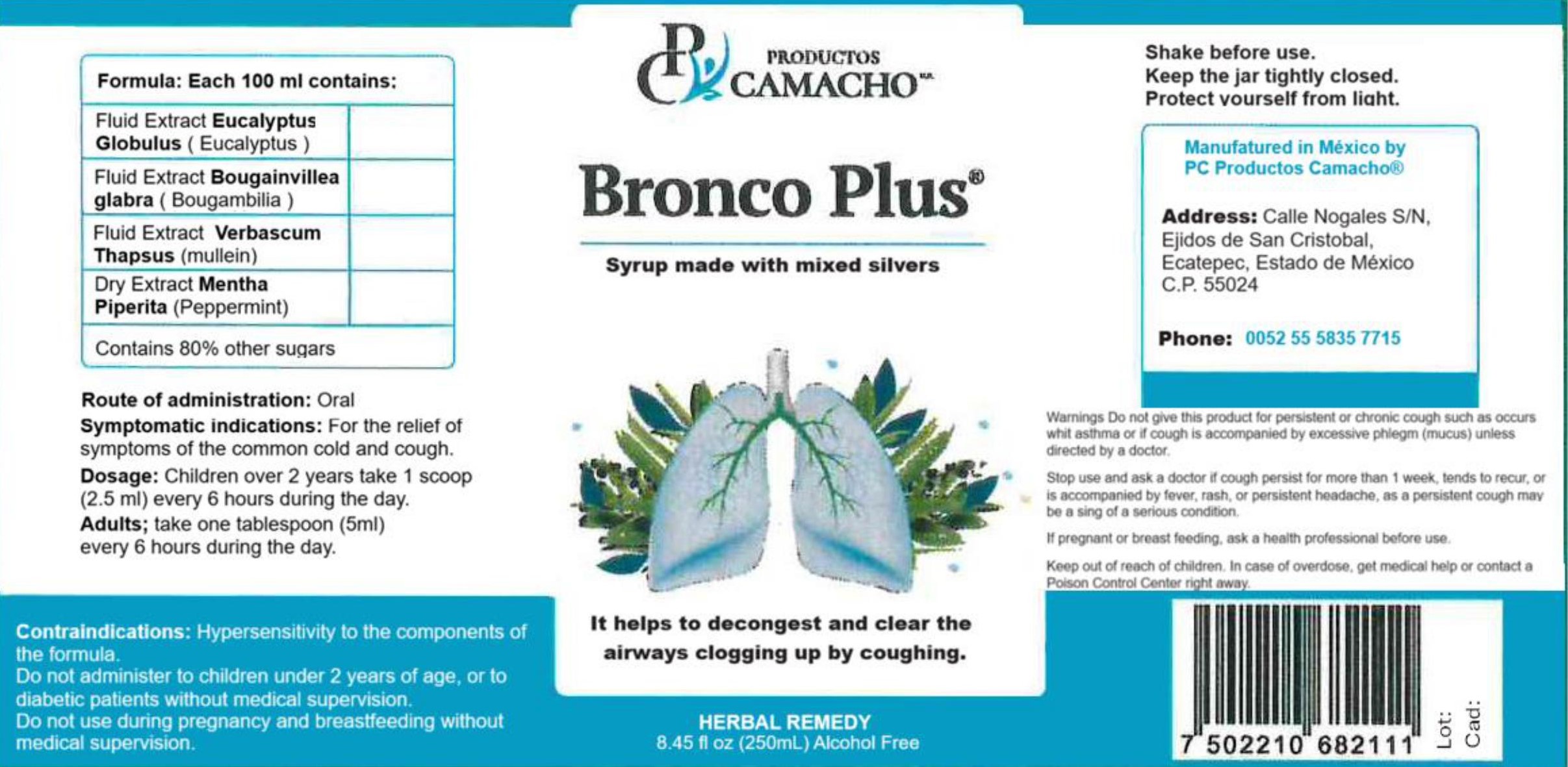 DRUG LABEL: BRONCO PLUS
NDC: 84370-202 | Form: SYRUP
Manufacturer: Camacho Navarrete, Jose Luis
Category: otc | Type: HUMAN OTC DRUG LABEL
Date: 20240106

ACTIVE INGREDIENTS: EUCALYPTUS GLOBULUS LEAF 0.0002 g/100 g
INACTIVE INGREDIENTS: WATER; VERBASCUM THAPSUS 0.002 g/100 g; INVERT SUGAR 80 g/100 g; MENTHA PIPERITA 0.002 g/100 g; BOUGAINVILLEA GLABRA FLOWER 0.0002 g/100 g

WARNINGS

Do not give this product for persistent or chronic cough such as occurs with asthma or if cough is accompanied by excesive phlegm (mucus) unles directed by a doctor.
Stop use and ask a doctor if cough persist for more than 1 week, tends to recur or is accompanied by fever, rash or persistent headache, as a persistent cough may be a sing of a serious condition.
If pregnant or breast feeding, ask a health professional before use.

INDICATIONS AND USAGE

For the relief of the symptoms of the common cold and cough.

DOSAGE AND ADMINISTRATION

Children over 2 years take one teaspoon (2.5 mL) every 6 hours during the day.
Adults: Take one jtablespoon (5 mL) every 6 hours during the day.

DOSAGE FORMS AND STRENGTHS

Oral administration.

CONTRAINDICATIONS

Hypersensitivity to the components of the formula.
Do not administer to children under 2 years of age, or to diabetic patients without medical supervision.
Do not use during pregnancy and breastfeeding without medical supervision.

Keep out of reach of children. In case of overdose, get medial help or contact a Poison Control Center right away.

PREGNANCY OR BREAST FEEDING

If pregnant or breast feeding, ask a health professional before use.

ACTIVE INGREDIENT

EUCALYPTUS GLOBULUS LEAF

INACTIVE INGREDIENT

WATER

BOUGAINVILLEA GLABRA FLOWER

MENTHA PIPERITA

VERBASCUM THAPSUS

INVERT SUGAR

PURPOSE

For the relief of the symptoms of the common cold and cough.

PACKAGE LABEL

84370-202-01